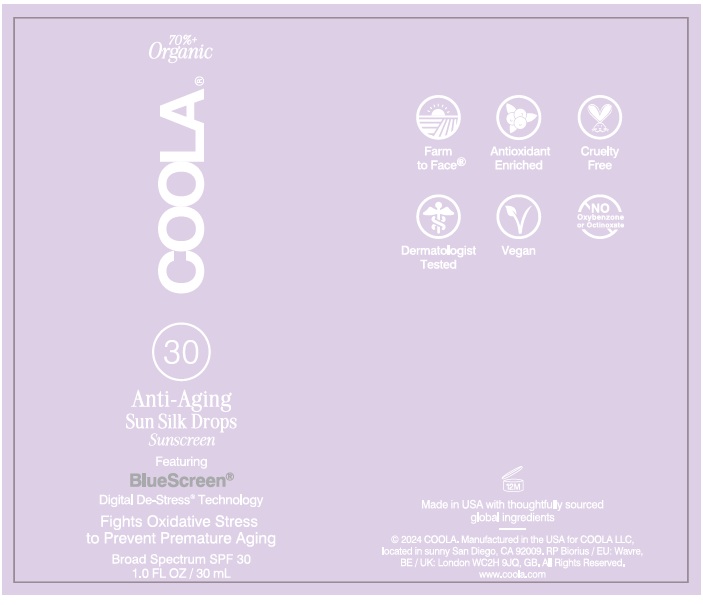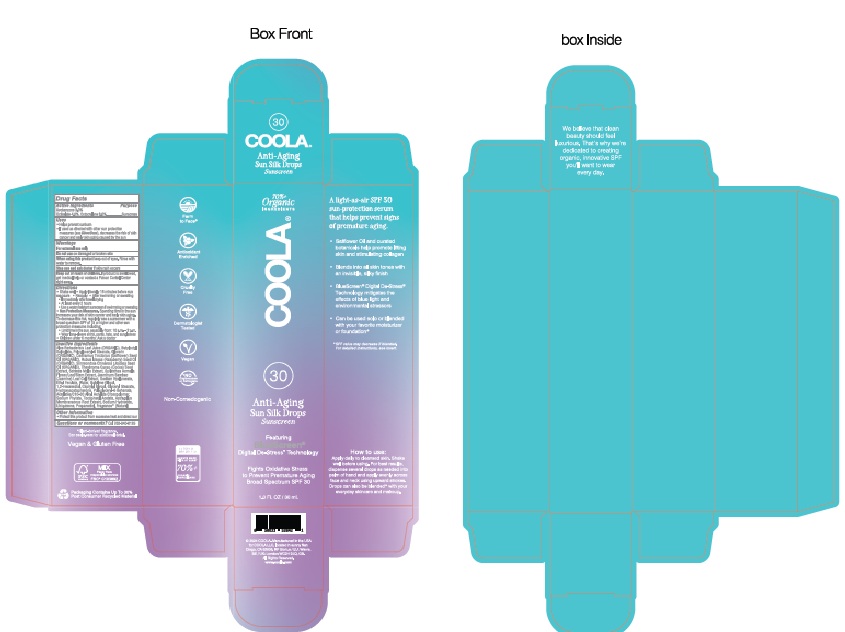 DRUG LABEL: COOLA Anti-Aging Sun Silk Drops Sunscreen
NDC: 79753-084 | Form: LIQUID
Manufacturer: COOLA LLC
Category: otc | Type: HUMAN OTC DRUG LABEL
Date: 20250107

ACTIVE INGREDIENTS: AVOBENZONE 3.0 g/100 mL; OCTISALATE 4.0 g/100 mL; OCTOCRYLENE 8.0 g/100 mL
INACTIVE INGREDIENTS: ALOE BARBADENSIS LEAF JUICE; BUTYLOCTYL SALICYLATE; POLYGLYCERYL-6 STEARATE; GLYCERIN; CARTHAMUS TINCTORIUS (SAFFLOWER) SEED OIL; RUBUS IDAEUS (RASPBERRY) SEED OIL; SIMMONDSIA CHINENSIS (JOJOBA) SEED OIL; COCOA; SCHINUS MOLLE OIL; BLAINVILLEA ACMELLA FLOWERING TOP; JASMINUM SAMBAC (JASMINE) FLOWER OIL; SODIUM HYALURONATE; ETHYL FERULATE; WATER; BUTYLENE GLYCOL; 1,2-HEXANEDIOL; CAPRYLYL GLYCOL; GLYCERYL STEARATE; HYDROXYACETOPHENONE; POLYGLYCERYL-6 BEHENATE; ACRYLATES/C10-30 ALKYL ACRYLATE CROSSPOLYMER (60000 MPA.S); SODIUM PHYTATE; .ALPHA.-TOCOPHEROL ACETATE; ASTRAGALUS MONGHOLICUS ROOT; SODIUM HYDROXIDE; UBIQUINONE; PROPANEDIOL

COOLA Anti-Aging Sun Silk Drops Sunscreen SPF 30

Active Ingredients

AVOBENZONE 3.0%, OCTISALATE 4.0%, OCTOCRYLENE 8.0%

Purpose

Sunscreen

Uses
• Helps prevent sunburn
• If used as directed with other sun protection
measures (see Directions) decreases the risk of
skin cancer and early aging caused by the sun

Warnings

For external use only

Do not use on damaged or broken skin

When using this product keep out of eyes. Rinse with water to remove

Stop use and ask doctor if skin rash occurs

Keep out of reach of children. If product is swallowed, get medical help or contact a Poison Control Center right away.

Directions

● Shake well ● Apply liberally 15 minutes before sun

exposure ● Reapply: ● After swimming or sweating

● Sun Protection Measures. Spending time in the sun increases

your risk of skin cancer and early aging. To decrease this

risk, regularly use a sunscreen with a broad spectrum SPF of 15

or higher and other sun protection measures including:
● Limit time in the sun, especially from: 10 a.m. – 2 p.m.
● Wear long-sleve shirts, pants, hats, and sunglasses

● Children under 6 months: Ask a doctor

Inactive Ingredients

Aloe Barbadensis Leaf Juice (ORGANIC), Butyloctyl

Salicylate, Polyglyceryl-6 Stearate, Glycerin

(ORGANIC), Carthamus Tinctorius (Safflower) Seed

Oil (ORGANIC), Rubus Idaeus (Raspberry) Seed Oil

(ORGANIC), Simmondsia Chinensis (Jojoba) Seed

Oil (ORGANIC), Theobroma Cacao (Cocoa) Seed

Extract, Schinus Molle Extract, Spilanthes Acmella

Flower/Leaf/Stem Extrqact, Jasminum Sambac

(Jasmine) Leaf Cell Extract, Sodium Hyaluronate,

Ethyl Ferulate, Water, Butylene Glycol,

1,2-Hexanediol, Caprylyl Glycol, Glyceryl Stearate,

Hydroxyacetophenone, Polyglyceryl-6 Behenate,

Acrylates/C10-30 Alkyl Acrylate Crosspolymer,

Sodium Phytate, Tocopheryl Acetate, Astragalus

Membranaceus Root Extract, Sodium Hydroxide,

Ubiquinone, Propanediol, Fragrance* (Natural)

Other Information

● Protect this product from excessive heat and direct sun

Questions or comments? Call 760-940-2125

Product Labeling: COOLA Anti-Aging Sun Silk Drops Sunscreen SPF 30

COOLA

Anti-Aging

Sun Silk Drops

Sunscreen

30

1.0 FL OZ / 30 mL

©2024 COOLA. Manufactured in the USA for COOLA LLC,

located in Sunny San Diego, CA 92009.

All Rights Reserved.

www.coola.com

CARTON

BOTTLE

res